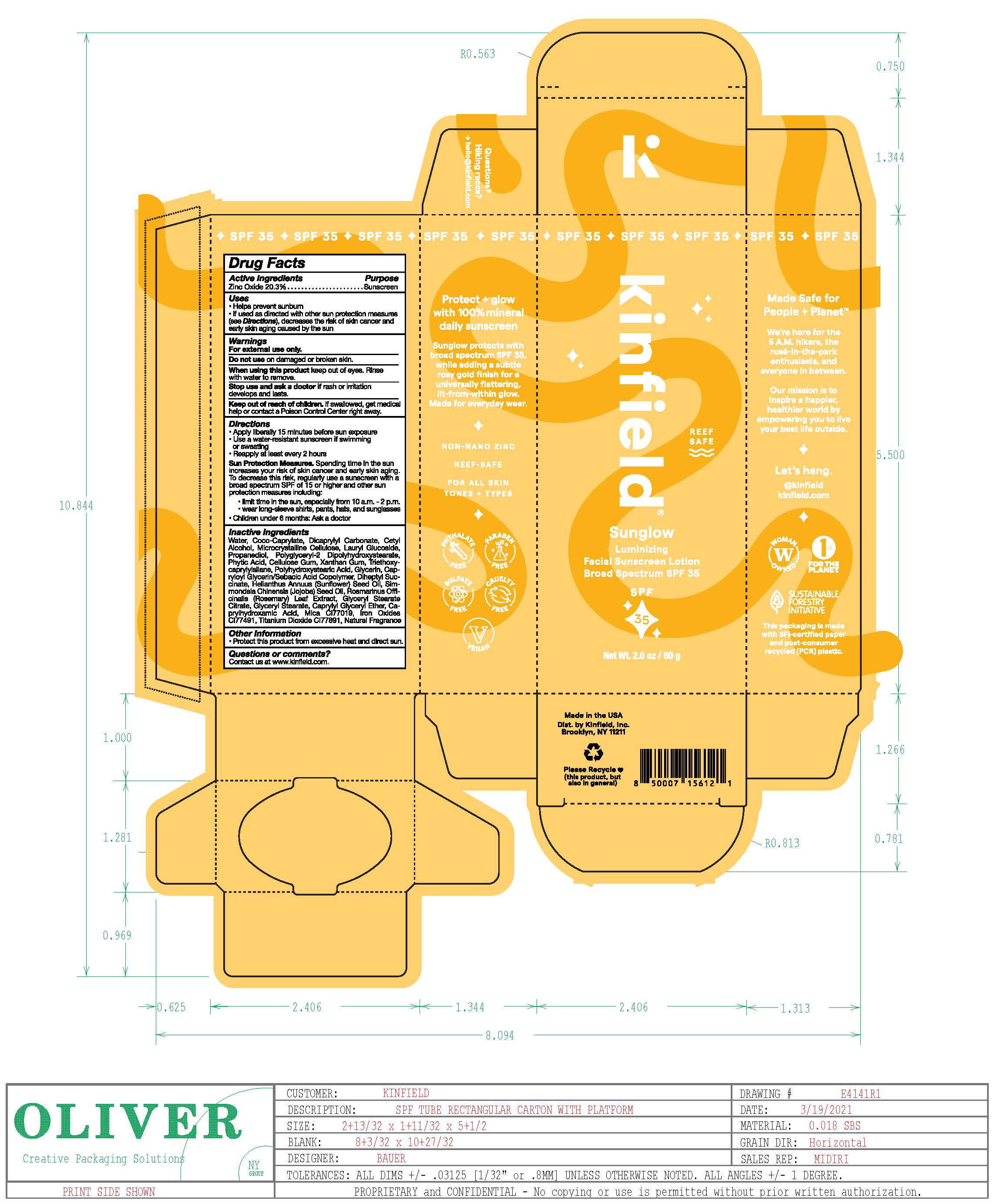 DRUG LABEL: Kinfield Sunglow Luminizing Facial Sunscreen Broad Spectrum SPF 35
NDC: 81750-050 | Form: LOTION
Manufacturer: Kinfield, Inc.
Category: otc | Type: HUMAN OTC DRUG LABEL
Date: 20251230

ACTIVE INGREDIENTS: ZINC OXIDE 20.3 g/100 g
INACTIVE INGREDIENTS: WATER; COCO-CAPRYLATE; DICAPRYLYL CARBONATE; CETYL ALCOHOL; MICROCRYSTALLINE CELLULOSE; LAURYL GLUCOSIDE; PROPANEDIOL; POLYGLYCERYL-2 DIPOLYHYDROXYSTEARATE; PHYTANIC ACID; CELLULOSE ACETATE; XANTHAN GUM; TRIETHOXYCAPRYLYLSILANE; POLYHYDROXYSTEARIC ACID (2300 MW); GLYCERIN; DIHEPTYL SUCCINATE; CAPRYLOYL GLYCERIN/SEBACIC ACID COPOLYMER (2000 MPA.S); HELIANTHUS ANNUUS WHOLE; SIMMONDSIA CHINENSIS SEED; ROSMARINUS OFFICINALIS WHOLE; GLYCERYL STEARATE CITRATE; GLYCERYL STEARATE SE; CAPRYLYL GLYCERYL ETHER; CAPRYLHYDROXAMIC ACID; MICA; TITANIUM DIHYDRIDE; BROWN IRON OXIDE

DRUG FACTS

Active Ingredients

Zinc Oxide 20.3%

Uses

• helps prevent sunburn • if used as directed with other
sun protection measures (see Directions), decreases the
risk of skin cancer and early skin aging caused by the sun

Warnings

For external use only
Do not use on damaged or broken skin.
When using this product keep out of eyes. Rinse with water to remove.
Stop use and ask a docor if rash occurs
Keep out of reach of children. If swalled, get medical help or contact a Poison Control Center right away.

Directions

• apply liberally 15 minutes before sun exposure
• reapply:
• Use a water resistant sunscreen if swimming or sweating
• Reapply at least every 2 hours
• Sun Protection Measures. Spending time in the sun increases your risk
of skin cancer and early skin aging. To decrease this risk, regularly use
a sunscreen with a broad spectrum SPF of 15 or higher and other sun
protection measures including:
• limit time in the sun, especially from 10 a.m. – 2 p.m.
• wear long-sleeve shirts, pants, hats, and sunglasses
• children under 6 months: Ask a doctor

Inactive ingredients

Water, Coco-Caprylate, Dicaprylyl Carbonate, Cetyl Alcohol, Microcrystalline Cellulose, Lauryl Glucoside, Propanediol, Polyglyceryl-2 Dipolyhydroxystearate, Phytic Acid, Cellulose Gum, Xanthan Gum, Triethoxycaprylylsilane, Polyhydroxystearic Acid, Glycerin, Capryloyl Glycerin/Sebacic Acid Copolymer, Diheptyl Succinate, Helianthus Annuus (Sunflower) Seed Oil, Simmondsia Chinensis (Jojoba) Seed Oil, Rosmarinus Officinalis (Rosemary) Leaf Extract, Glyceryl Stearate Citrate, Glyceryl Stearate, Caprylyl Glyceryl Ether, Caprylhydroxamic Acid, Mica, Iron Oxides, Titanium Dioxide, Fragrance

Other Information

• protect the product in this container from excessive
heat and direct sun

Questions or Comments?

Conctact us at www.kinfield.com

Keep out of reach of children. If product is swallowed, get medical help or contact a Poison Control Center right away.

Purpose

Purpose: Sunscreen